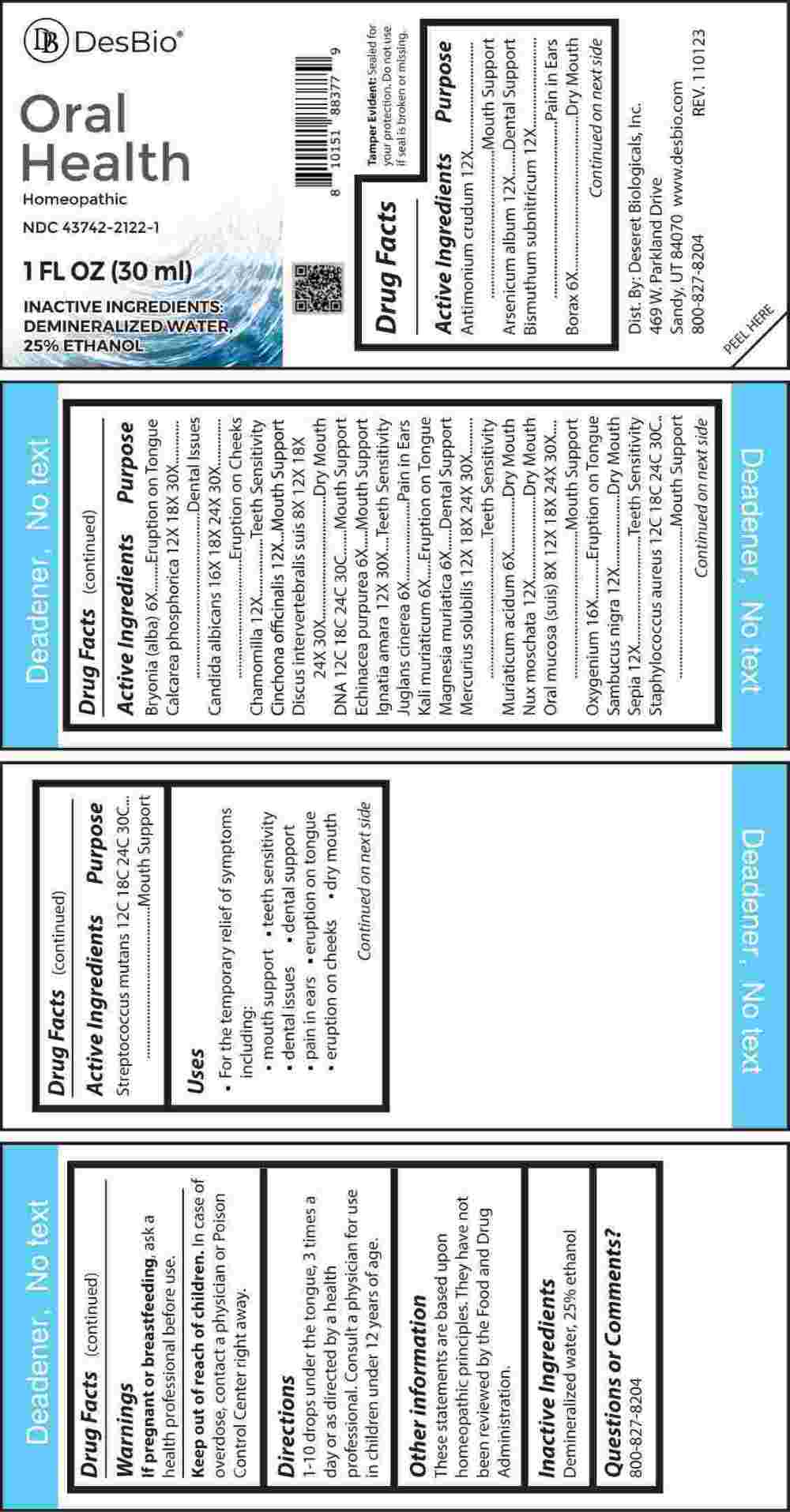 DRUG LABEL: Oral Health
NDC: 43742-2122 | Form: LIQUID
Manufacturer: Deseret Biologicals, Inc.
Category: homeopathic | Type: HUMAN OTC DRUG LABEL
Date: 20240401

ACTIVE INGREDIENTS: ANTIMONY TRISULFIDE 12 [hp_X]/1 mL; ARSENIC TRIOXIDE 12 [hp_X]/1 mL; BISMUTH SUBNITRATE 12 [hp_X]/1 mL; SODIUM BORATE 6 [hp_X]/1 mL; BRYONIA ALBA ROOT 6 [hp_X]/1 mL; TRIBASIC CALCIUM PHOSPHATE 12 [hp_X]/1 mL; CANDIDA ALBICANS 16 [hp_X]/1 mL; MATRICARIA CHAMOMILLA WHOLE 12 [hp_X]/1 mL; CINCHONA OFFICINALIS BARK 12 [hp_X]/1 mL; SUS SCROFA INTERVERTEBRAL DISC 8 [hp_X]/1 mL; HERRING SPERM DNA 12 [hp_C]/1 mL; ECHINACEA PURPUREA WHOLE 6 [hp_X]/1 mL; STRYCHNOS IGNATII SEED 12 [hp_X]/1 mL; JUGLANS CINEREA BRANCH BARK/ROOT BARK 6 [hp_X]/1 mL; POTASSIUM CHLORIDE 6 [hp_X]/1 mL; MAGNESIUM CHLORIDE 6 [hp_X]/1 mL; MERCURIUS SOLUBILIS 12 [hp_X]/1 mL; HYDROCHLORIC ACID 6 [hp_X]/1 mL; NUTMEG 12 [hp_X]/1 mL; SUS SCROFA ORAL MUCOSA 8 [hp_X]/1 mL; OXYGEN 16 [hp_X]/1 mL; SAMBUCUS NIGRA FLOWERING TOP 12 [hp_X]/1 mL; SEPIA OFFICINALIS JUICE 12 [hp_X]/1 mL; STAPHYLOCOCCUS AUREUS 12 [hp_C]/1 mL; STREPTOCOCCUS MUTANS 12 [hp_C]/1 mL
INACTIVE INGREDIENTS: WATER; ALCOHOL

DRUG FACTS:

ACTIVE INGREDIENTS:

Antimonium Crudum 12X, Arsenicum Album 12X, Bismuthum Subnitricum 12X, Borax 6X, Bryonia (Alba) 6X, Calcarea Phosphorica 12X, 18X, 30X, Candida Albicans 16X, 18X, 24X, 30X, Chamomilla 12X, Cinchona Officinalis 12X, Discus Intervertebralis Suis 8X, 12X, 18X, 24X, 30X, DNA 12C, 18C, 24C, 30C, Echinacea Purpurea 6X, Ignatia Amara 12X, 30X, Juglans Cinerea 6X, Kali Muriaticum 6X, Magnesia Muriatica 6X, Mercurius Solubilis 12X, 18X, 24X, 30X, Muriaticum Acidum 6X, Nux Moschata 12X, Oral Mucosa (Suis) 8X, 12X, 18X, 24X, 30X, Oxygenium 16X, Sambucus Nigra 12X, Sepia 12X, Staphylococcus Aureus 12C, 18C, 24C, 30C, Streptococcus Mutans 12C, 18C, 24C, 30C.

PURPOSE:

Antimonium Crudum – Mouth Support, Arsenicum Album – Dental Support, Bismuthum Subnitricum – Pain in Ears, Borax – Dry Mouth, Bryonia (Alba) – Eruption on Tongue, Calcarea Phosphorica – Dental Issues, Candida Albicans – Eruption on Cheeks, Chamomilla – Teeth Sensitivity, Cinchona Officinalis – Mouth Support, Discus Intervertebralis Suis – Dry Mouth, DNA – Mouth Support, Echinacea Purpurea – Mouth Support, Ignatia Amara – Teeth Sensitivity, Juglans Cinerea – Pain in Ears, Kali Muriaticum – Eruption on Tongue, Magnesia Muriatica – Dental Support, Mercurius Solubilis – Teeth Sensitivity, Muriaticum Acidum – Dry Mouth, Nux Moschata – Dry Mouth, Oral Mucosa (Suis) – Mouth Support, Oxygenium – Eruption on Tongue, Sambucus Nigra – Dry Mouth, Sepia – Teeth Sensitivity, Staphylococcus Aureus – Mouth Support, Streptococcus Mutans – Mouth Support

USES:

• For the temporary relief of symptoms including:

• mouth support • teeth sensitivity • dental issues

• dental support • pain in ears • eruption on tongue

• eruption on cheeks • dry mouth

These statements are based upon homeopathic principles. They have not been reviewed by the Food and Drug Administration.

WARNINGS:

If pregnant or breast-feeding, ask a health professional before use.

Keep out of reach of children. In case of overdose, contact a physician or Poison Control Center right away.

Tamper Evident: Sealed for your protection. Do not use if seal is broken or missing.

KEEP OUT OF REACH OF CHILDREN:

In case of overdose, contact a physician or Poison Control Center right away.

DIRECTIONS:

1-10 drops under the tongue, 3 times a day or as directed by a health professional. Consult a physician for use in children under 12 years of age.

INACTIVE INGREDIENTS:

Demineralized water, 25% ethanol

QUESTIONS:

Dist. By: Deseret Biologicals, Inc.

469 W. Parkland Drive

Sandy, UT 84070

www.desbio.com

800-827-8204

PACKAGE LABEL DISPLAY:

DesBio

Oral Health

Homeopathic
NDC 43742-2122-1
1 FL OZ (30 ml)